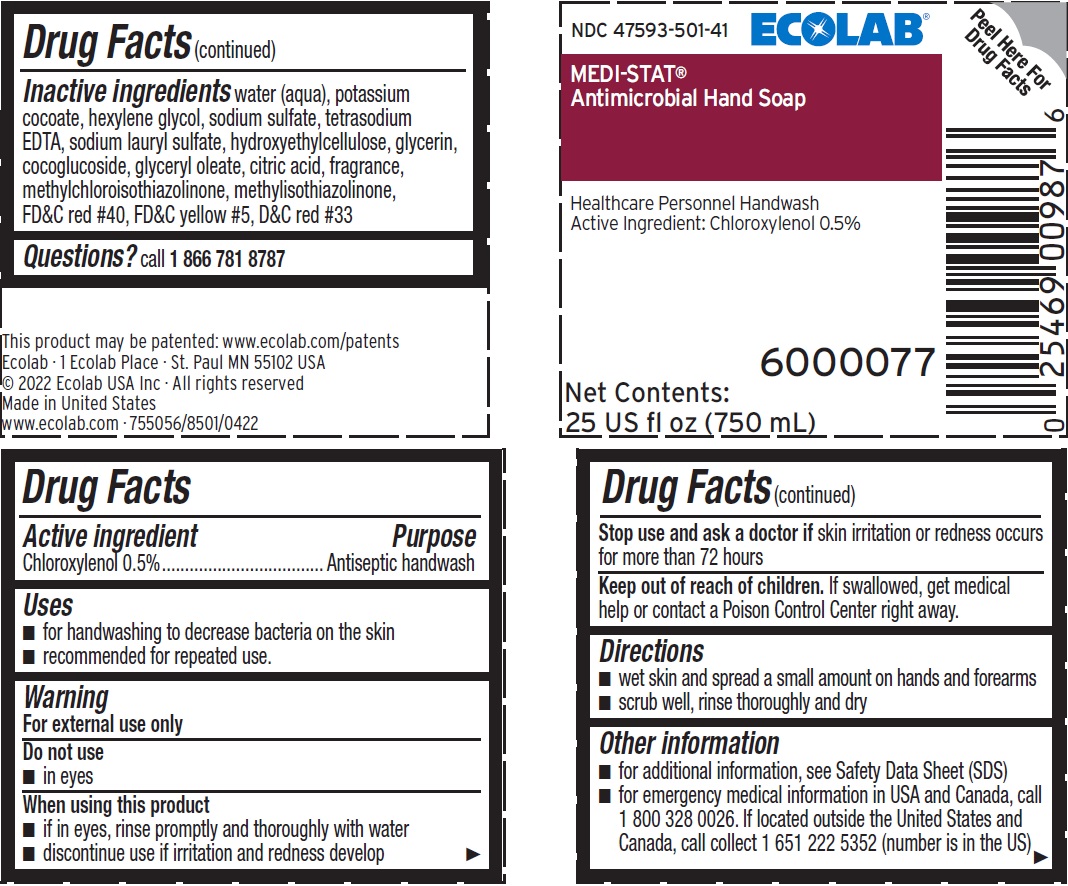 DRUG LABEL: Ecolab
NDC: 47593-501 | Form: SOLUTION
Manufacturer: Ecolab Inc.
Category: otc | Type: HUMAN OTC DRUG LABEL
Date: 20240508

ACTIVE INGREDIENTS: CHLOROXYLENOL 5.20 mg/1 mL
INACTIVE INGREDIENTS: WATER; POTASSIUM COCOATE; HEXYLENE GLYCOL; SODIUM SULFATE; EDETATE SODIUM; SODIUM LAURYL SULFATE; HYDROXYETHYL CELLULOSE (3000 CPS AT 1%); GLYCERIN; COCO GLUCOSIDE; GLYCERYL OLEATE; CITRIC ACID MONOHYDRATE; METHYLCHLOROISOTHIAZOLINONE; METHYLISOTHIAZOLINONE; FD&C RED NO. 40; FD&C YELLOW NO. 5; D&C RED NO. 33

Drug Facts

Active ingredient

Chloroxylenol 0.5%

Purpose

Antiseptic handwash

Uses

- For handwashing to decrease bacteria on the skin
- recommended for repeated use.

Warnings

For external use only

Do not use

- In eyes

When using this product

- If in eyes, rinse promptly and thoroughly with water
- Discontinue use if irritation and redness develop

Stop use and ask a doctor if skin irritation or redness occurs for more than 72 hours

Keep out of reach of children. If swallowed, get medical help or contact a Poison Control Center right away.

Directions

- Wet skin and spread a small amount on hands and forearms
- Scrub well, rinse thoroughly and dry

Other information

- for additional information, see Safety Data Sheet (SDS)
- for emergency medical information in USA and Canada, call 1 800 328 0026. If located outside the United States and Canada, call collect 1 651 222 5352 (number is in the US)

INACTIVE INGREDIENT

Inactive ingredients water (aqua), potassium cocoate, hexylene glycol, sodium sulfate, tetrasodium EDTA, sodium lauryl sulfate, hydroxyethylcellulose, glycerin, cocoglucoside, glyceryl oleate, citric acid, frangrance, methylchloroisothiazolinone, methylisothiazolinone, FD&C red #40, FD&C yellow #5, D&C red #33

Questions? call 1 866 781 8787

Principal display panel and representative label

NDC 47593-501-41 ECOLAB

Medi-Stat

Antimicrobial Hand Soap

Healthcare Personnel Handwash

Active Ingredient: Chloroxylenol 0.5%

6000077

Net Contents:

25 US fl oz (750 mL)

Ecolab · 1 Ecolab Place · St. Paul MN 55102 USA

© 2022 Ecolab USA Inc · All rights reserved

Made in United States

www.ecolab.com · 755056/8501/0422